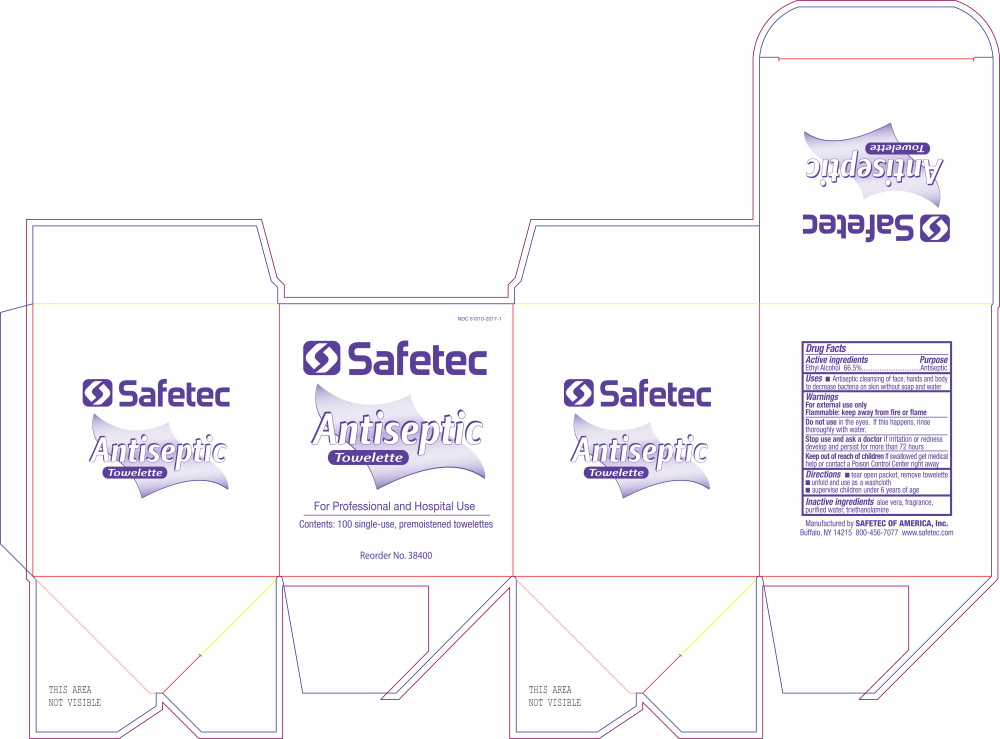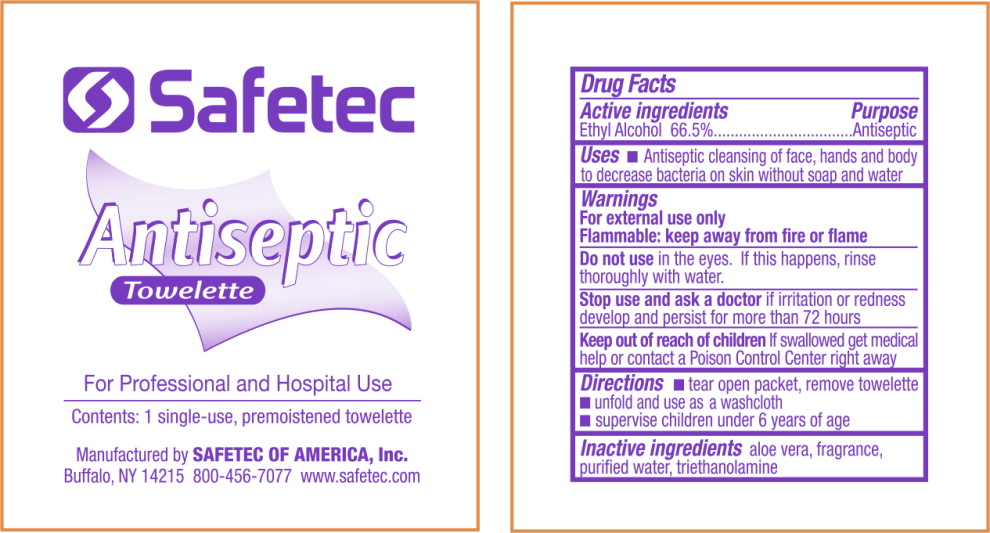 DRUG LABEL: Antiseptic
NDC: 61010-2017 | Form: CLOTH
Manufacturer: Safetec of America, Inc.
Category: otc | Type: HUMAN OTC DRUG LABEL
Date: 20240205

ACTIVE INGREDIENTS: ALCOHOL 665 mL/1 L
INACTIVE INGREDIENTS: ALOE VERA LEAF; WATER; TROLAMINE

61010-2017 . Topical antiseptic wipe

Drug Facts

Active ingredients

Ethyl Alcohol 66.5%

Purpose

Antiseptic

Uses

- Antiseptic cleansing of face, hands and body to decrease bacteria on skin without soap and water

Warnings

For external use only

Flammable: keep away from fire or flame

DO NOT USE

Do not usein the eyes. If this happens, rinse thoroughly with water.

Stop use and ask a doctorif irritation or redness develop and persist for more than 72 hours

KEEP OUT OF REACH OF CHILDREN

Keep out of reach of childrenIf swallowed get medical help or contact a Poison Control Center right away

Directions

- tear open packet, remove towelette
- unfold and use as a washcloth
- supervise children under 6 years of age

Inactive ingredients

aloe vera, fragrance, purified water, triethanolamine

Principal Display Panel - Safetec Antiseptic Towelette Carton Label

NDC 61010-2017-1

Safetec

Antiseptic
Towelette

For Professional and Hospital Use

Contents: 100 single-use, premoistened towelettes

Reorder No. 38400

Principal Display Panel - Safetec Antiseptic Towelette Packet Label

Safetec

Antiseptic
Towelette

For Professional and Hospital Use

Contents: 1 single-use, premoistened towelette

Manufactured by SAFETEC OF AMERICA, Inc.

Buffalo, NY 14215 800-456-7077 www.safetec.com